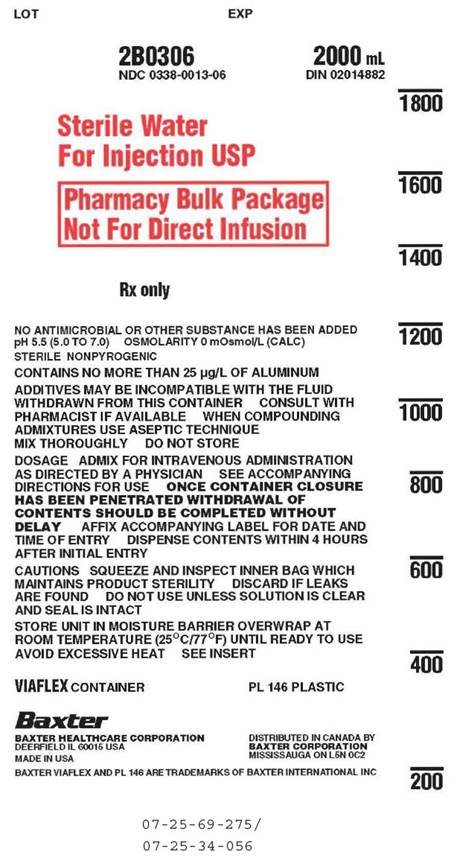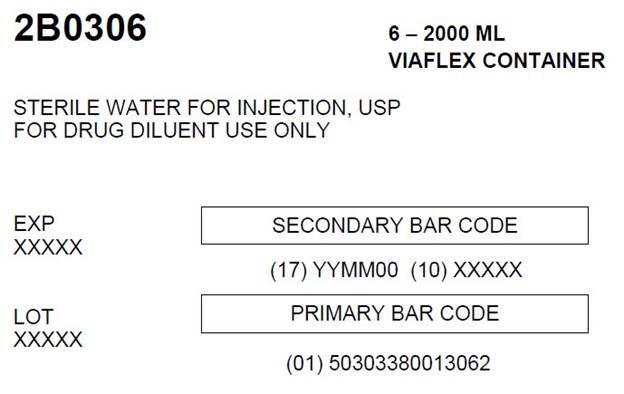 DRUG LABEL: Sterile Water
NDC: 0338-0013 | Form: INJECTION, SOLUTION
Manufacturer: Baxter Healthcare Company
Category: prescription | Type: HUMAN PRESCRIPTION DRUG LABEL
Date: 20160531

ACTIVE INGREDIENTS: WATER 100 mL/100 mL

Sterile Water For Injection, USP
Pharmacy Bulk Package
Not for Direct Infusion
VIAFLEX Plastic Container

DESCRIPTION

Sterile Water for Injection, USP is sterile, nonpyrogenic, distilled water in a Pharmacy Bulk Package. A Pharmacy Bulk Package is a container of a sterile preparation for parenteral use that contains many single doses. The contents are intended for use in a pharmacy admixture program and are restricted to the preparation of admixtures for intravenous infusion. No antimicrobial or other substance has been added. pH 5.5 (5.0 to 7.0). Osmolarity O mOsmol/L (calc.).

The VIAFLEX plastic container is fabricated from a specially formulated polyvinyl chloride (PL 146 Plastic). Exposure to temperatures above 25°C/77°F during transport and storage will lead to minor losses in moisture content. Higher temperatures lead to greater losses. It is unlikely that these minor losses will lead to clinically significant changes within the expiration period. The amount of water that can permeate from inside the container into the overwrap is insufficient to affect the solution significantly. Solutions in contact with the plastic container may leach out certain chemical components from the plastic in very small amounts; however, biological testing was supportive of the safety of the plastic container materials.

CLINICAL PHARMACOLOGY

Sterile Water for Injection, USP is used for fluid replacement only after suitable admixing to approximate isotonicity.

INDICATIONS AND USAGE

Sterile Water for Injection, USP is indicated in the aseptic preparation of parenteral admixtures.

CONTRAINDICATIONS

Sterile Water for Injection, USP is a hemolytic agent due to its hypotonicity. Therefore, it is contraindicated for intravenous administration without admixing.

WARNINGS

This solution is for compounding only, not for direct infusion. Hemolysis may occur following infusion of Sterile Water for Injection, USP. Hemoglobin induced renal failure has been reported following hemolysis.

WARNING: This product contains aluminum that may be toxic. Aluminum may reach toxic levels with prolonged parenteral administration if kidney function is impaired. Premature neonates are particularly at risk because their kidneys are immature, and they require large amounts of calcium and phosphate solutions, which contain aluminum.

Research indicates that patients with impaired kidney function, including premature neonates, who receive parenteral levels of aluminum at greater than 4 to 5 µg/kg/day accumulate aluminum at levels associated with central nervous system and bone toxicity. Tissue loading may occur at even lower rates of administration.

PRECAUTIONS

Do not use unless solution is clear and seal is intact.

Drug product contains no more than 25 µg/L of aluminum.

Pediatric Use:

Safety and effectiveness have been established in pediatric patients. However, in neonates or very small infants the volume of fluid may affect fluid and electrolyte balance.

ADVERSE REACTIONS

The administration of a suitable admixture of prescribed drugs may be associated with adverse reactions because of the solution or the technique of administration including febrile response, infection at the site of injection, venous thrombosis or phlebitis extending from the site of injection, extravasation and hypervolemia. If an adverse reaction does occur, discontinue the infusion, evaluate the patient, institute appropriate therapeutic countermeasures and save the remainder of the fluid for examination if deemed necessary.

DOSAGE AND ADMINISTRATION

Following suitable admixture of prescribed drugs, the dosage is usually dependent upon the age, weight and clinical condition of the patient as well as laboratory determinations. See directions accompanying drugs.

Parenteral drug products should be inspected visually for particulate matter and discoloration prior to administration whenever solution and container permit. Use of a final filter is recommended during administration of all parenteral solutions where possible.

Sterile Water for Injection, USP in the Pharmacy Bulk Package is intended for use in the preparation of sterile, intravenous admixtures. Additives may be incompatible with the fluid withdrawn from this container. Complete information is not available. Those additives known to be incompatible should not be used. Consult with pharmacist, if available. When compounding admixtures, use aseptic technique. Mix thoroughly. Do not store any unused portion of Sterile Water for Injection, USP.

DIRECTIONS FOR USE OF VIAFLEX PLASTIC PHARMACY BULK PACKAGE CONTAINER

To Open

Tear overwrap down side at slit and remove solution container. Visually inspect the container. If the outlet port protector is damaged, detached, or not present, discard container as solution path sterility may be impaired. Some opacity of the plastic due to moisture absorption during the sterilization process may be observed. This is normal and does not affect the solution quality or safety. The opacity will diminish gradually. Check for minute leaks by squeezing inner bag firmly, if leaks are found, discard solution as sterility may be impaired.

For compounding only, not for direct infusion.

Preparation for Admixing

1. The Pharmacy Bulk Package is to be used only in a suitable work area such as a laminar flow hood (or an equivalent clean air compounding area).
2. Suspend container from eyelet support.
3. Remove plastic protector from outlet port at bottom of container.
4. Attach solution transfer set. Refer to complete directions accompanying set.
  Note: The closure shall be penetrated only one time with a suitable sterile transfer device or dispensing set which allows measured dispensing of the contents.
5. VIAFLEX containers should not be written on directly since ink migration has not been investigated. Affix accompanying label for date and time of entry.
6. Once container closure has been penetrated, withdrawal of contents should be completed without delay. After initial entry, maintain contents at room temperature (25°C/77°F) and dispense within 4 hours.

HOW SUPPLIED

Sterile Water for Injection, USP is supplied in a VIAFLEX plastic Pharmacy Bulk Package container as follows:

2000 mL | 2B0306 | NDC 0338-0013-06
3000 mL | 2B0307 | NDC 0338-0013-08
5000 mL | 2B0309 | NDC 0338-0013-29

Exposure of pharmaceutical products to heat should be minimized. Avoid excessive heat. It is recommended the product be stored at room temperature (25°C/77°F).

Baxter Healthcare Corporation
Deerfield, IL 60015 USA

Printed in USA

Baxter, Viaflex, and PL 146 are trademarks of Baxter International Inc.

07 19 73 676

Rev. September 2014

Distributed in Canada by
Baxter Corporation
Mississauga, ON L5N 0C2

PACKAGE LABEL - PRINCIPLE DISPLAY PANEL

Container Label

Container Label

LOT EXP

2B0306 2000 mL
NDC 0338-0013-06 DIN 02014882

Sterile Water
For Injection USP

Pharmacy Bulk Package
Not For Direct Infusion

Rx Only

NO ANTIMICROBIAL OR OTHER SUBSTANCE HAS BEEN ADDED
pH 5.5 (5.0 TO 7.0) OSMOLARITY 0 mOsmol/L (CALC)
STERILE NONPYROGENIC

CONTAINS NO MORE THAN 25 μg/L OF ALUMINUM

ADDITIVES MAY BE INCOMPATIBLE WITH THE FLUID
WITHDRAWN FROM THIS CONTAINER CONSULT WITH
PHARMACIST IF AVAILABLE WHEN COMPOUNDING
ADMIXTURES USE ASEPTIC TECHNIQUE
MIX THOROUGHLY DO NOT STORE

DOSAGE ADMIX FOR INTRAVENOUS ADMINISTRATION
AS DIRECTED BY A PHYSICIAN SEE ACCOMPANYING
DIRECTIONS FOR USE ONCE CONTAINER CLOSURE
HAS BEEN PENETRATED WITHDRAWAL OF
CONTENTS SHOULD BE COMPLETED WITHOUT
DELAY AFFIX ACCOMPANYING LABEL FOR DATE AND
TIME OF ENTRY DISPENSE CONTENTS WITHIN 4 HOURS
AFTER INITIAL ENTRY

CAUTIONS SQUEEZE AND INSPECT INNER BAG WHICH
MAINTAINS PRODUCT STERILITY DISCARD IF LEAKS
ARE FOUND DO NOT USE UNLESS SOLUTION IS CLEAR
AND SEAL IS INTACT

STORE UNIT IN MOISTURE BARRIER OVERWRAP AT
ROOM TEMPERATURE (25°C/77°F) UNTIL READY TO USE
AVOID EXCESSIVE HEAT SEE INSERT

VIAFLEX CONTAINER PL 146 PLASTIC

Baxter logo

BAXTER HEALTHCARE CORPORATION
DEERFIELD IL 60015 USA

MADE IN USA

DISTRIBUTED IN CANADA BY
BAXTER CORPORATION
MISSISSAUGA ON L5N 0C2

BAXTER PL 146 AND VIAFLEX ARE TRADEMARKS OF BAXTER INTERNATIONAL INC

1800

1600

1400

1200

1000

800

600

400

200

07-25-69-275/
07-25-34-056

Carton Label

Carton Label

2B0306 6 - 2000 ML
VIAFLEX CONTAINER

STERILE WATER FOR INJECTION, USP
FOR DRUG DILUENT USE ONLY

EXP
XXXXX

SECONDARY BAR CODE

(17) YYMM00 (10) XXXXX

LOT
XXXXX

PRIMARY BAR CODE

(01) 50303380013062